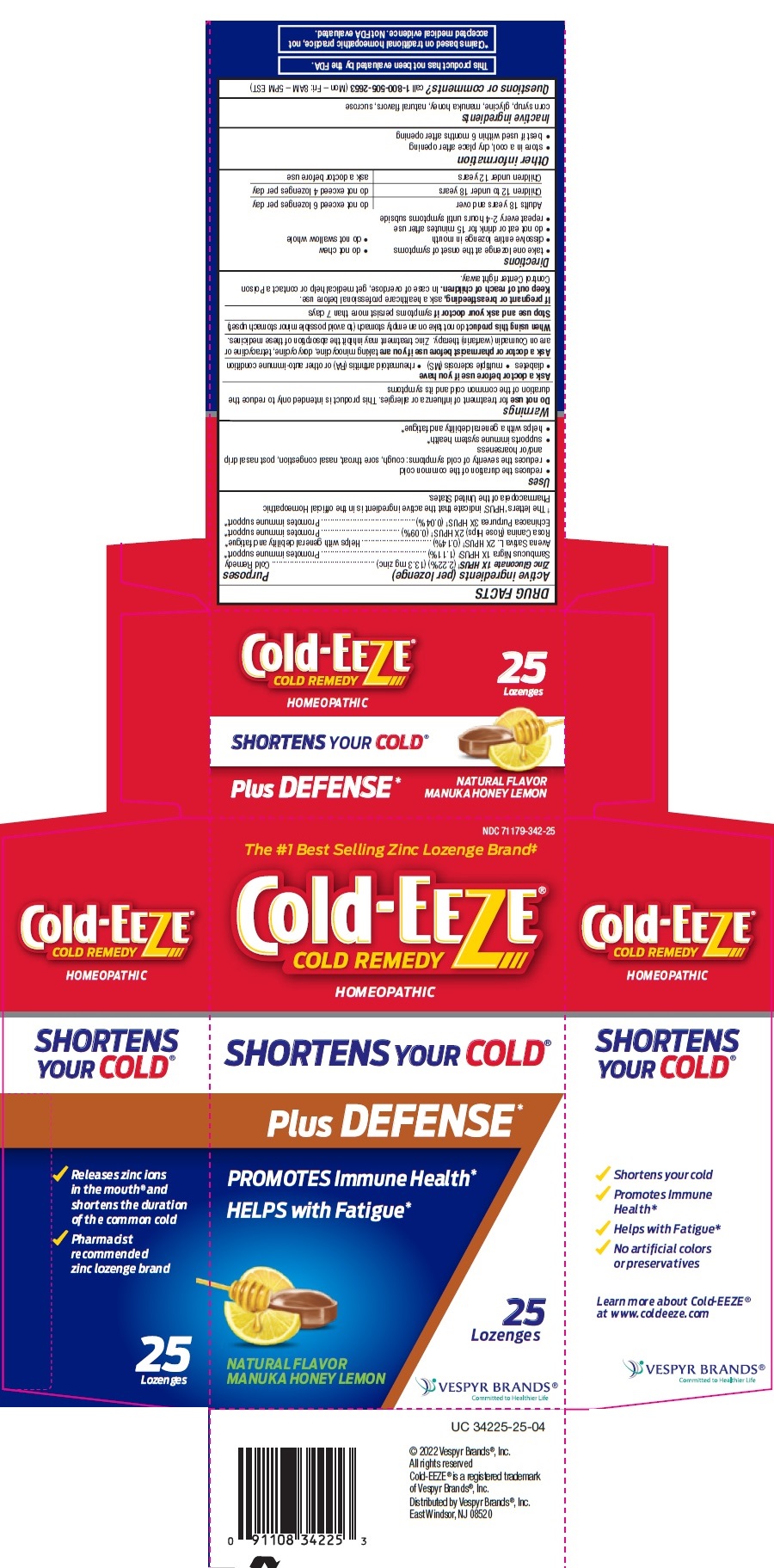 DRUG LABEL: Cold-EEZE Cold Remedy
NDC: 71179-342 | Form: LOZENGE
Manufacturer: Vespyr Brands Inc
Category: homeopathic | Type: HUMAN OTC DRUG LABEL
Date: 20250101

ACTIVE INGREDIENTS: ZINC GLUCONATE 13.3 mg/1 1; SAMBUCUS NIGRA FLOWER 50 mg/1 1; AVENA SATIVA FLOWERING TOP 6.2 mg/1 1; ECHINACEA PURPUREA 2 mg/1 1; ROSA CANINA FRUIT 4 mg/1 1
INACTIVE INGREDIENTS: HONEY; GLYCINE; SUCROSE; CORN SYRUP

Cold-EEZE Cold Remedy Plus DEFENSE* Manuka honey lemon

Active ingredients

Active ingredients (per lozenge) . . . . . . . . . . . . . . . . . . . . . . Purposes
Zinc Gluconate 1X HPUS† (2.22%) (13.3 mg zinc).................. Cold Remedy
Sambucus Nigra 1X HPUS† (1.11%) ......................................... Promotes immune support*
Avena Sativa L. 2X HPUS† (0.14%) ............................................ Helps with general debility and fatigue*

Rosa Canina (Rose Hips) 2X HPUS† (0.09%) ........................ Promotes immune support*

Echinacea Purpurea 3X HPUS† (0.04%) .................................. Promotes immune support*
† The letters ‘HPUS’ indicate that the active ingredient is in the official Homeopathic Pharmacopeia of the United States.

Purposes

Uses

- reduces the duration of the common cold
- reduces the severity of cold symptoms: cough, sore throat, nasal congestion, post nasal drip and/or hoarseness
- supports immune system health*
- helps with a general debility and fatigue*

Warnings

Do not use for treatment of influenza or allergies. This product is intended only to reduce the duration of the common cold and its symptoms.

Ask a doctor before use if you have
• diabetes • multiple sclerosis (MS) • rheumatoid arthritis (RA) or other auto-immune condition

Ask a doctor or pharmacist before use if you are taking minocycline, doxycycline, tetracycline or are on Coumadin (warfarin) therapy. Zinc treatment may inhibit the absorption of these medicines.

When using this product do not take on an empty stomach (to avoid possible minor stomach upset)

Stop use and ask your doctor if symptoms persist more than 7 days

PREGNANCY OR BREAST FEEDING

If pregnant or breastfeeding, ask a healthcare professional before use.

Keep out of reach of children. In case of overdose, get medical help or contact a Poison Control Center right away.

Directions

• take one lozenge at the onset of symptoms • do not chew
• dissolve entire lozenge in mouth • do not swallow whole
• do not eat or drink for 15 minutes after use
• repeat every 2-4 hours until symptoms subside

Adults 18 years and over | do not exceed 6 lozenges per day
Children 12 to under 18 years | do not exceed 4 lozenges per day
Children under 12 years | ask a doctor before use

Other information

- store in a cool, dry place after opening
- best if used within 6 months after opening

Inactive ingredients

corn syrup, glycine, manuka honey, natural flavors, sucrose

Questions or comments?

call 1-800-505-2653 (Mon – Fri: 8AM – 5PM EST)

PACKAGE LABEL

Cold-EEZE®

COLD REMEDY

HOMEOPATHIC

SHORTENS YOUR COLD®

Plus DEFENSE*

PROMOTES Immune Health*

HELPS with Fatigue*

NATURAL FLAVOR MANUKA HONEY LEMON

25 Lozenges

©2023 Vespyr Brands®, Inc.

All rights reserved

Cold-EEZE® is a registred trademark of Vespyr Brands®, Inc.

Distributed by Vespyr Brands®, Inc.

East Windsor, NJ 08520

This product has not been evaluated by the FDA

*Claims based on traditional homeopathic practice, not accepted medical evidence. Not FDA evaluated.